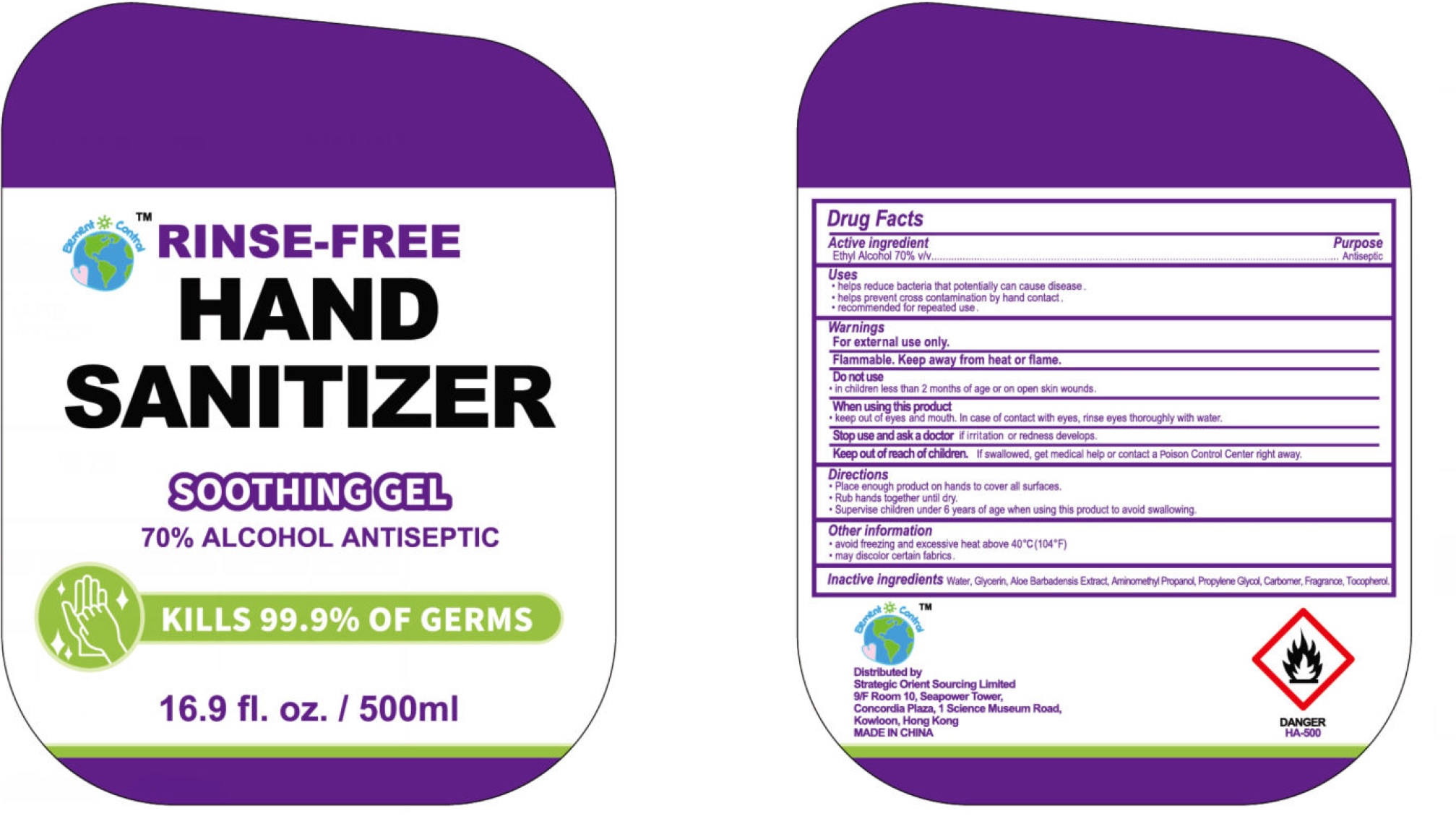 DRUG LABEL: Element Control Rinse Free Hand Sanitizer Soothing
NDC: 79995-027 | Form: GEL
Manufacturer: Strategic Orient Sourcing Limited
Category: otc | Type: HUMAN OTC DRUG LABEL
Date: 20200812

ACTIVE INGREDIENTS: ALCOHOL 0.7 mL/1 mL
INACTIVE INGREDIENTS: WATER; GLYCERIN; AMINOMETHYLPROPANOL; PROPYLENE GLYCOL; CARBOMER HOMOPOLYMER, UNSPECIFIED TYPE; TOCOPHEROL

Element Control Rinse-Free Hand Sanitizer Soothing Gel

Active ingredient

Ethyl Alcohol 70%

Purpose

Antiseptic

Use

- helps reduce bacteria that potentially can cause disease.
- helps prevent cross contamination by hand contact.
- recommended for repeated use.

Warnings

For external use only.

Flammable. Keep away from heat or flame.

Do not use

- in children less than 2 months of age or on open skin wounds.

When using this product

- keep out of eyes and mouth. In case of contact with eyes, rinse eyes thoroughly with water.

Stop use and ask a doctor

- if irritation and redness develop

Keep out of reach of children.

If swallowed, get medical help or contact a Poison Control Center right away.

Directions

- Place enough product on hands to cover all surfaces.
- Rub hands together until dry.
- Supervise children under 6 years of age when using this product to avoid swallowing.

Other information

- avoid freezing and excessive heat above 40°C (104°F)
- may discolor certain fabrics.

Inactive ingredients

Water, Glycerin, Aloe Barbadensis Extract, Aminomethyl Propanol, Propylene Glycol, Carbomer, Fragrance, Tocopherol.